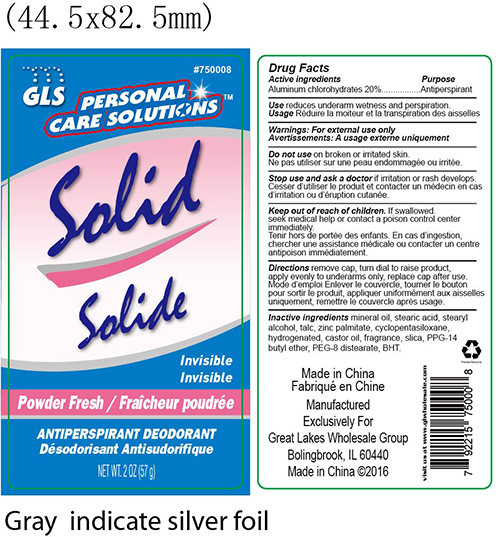 DRUG LABEL: antiperspirant
NDC: 64092-208 | Form: STICK
Manufacturer: Great Lakes Wholesale, Marketing and Sales, Inc
Category: otc | Type: HUMAN OTC DRUG LABEL
Date: 20160805

ACTIVE INGREDIENTS: ALUMINUM CHLOROHYDRATE 11.4 1/57 g
INACTIVE INGREDIENTS: MINERAL OIL

DESCRIPTION

GLS PERSONAL CARE SOLUTIONS

Solid Invisible

Powder Fresh

Antiperspirant Deodorant

Net WT. 2 OZ (57 g)

Active Ingredients Purpose

Aluminum chlorohydrates 20%............................Antiperspirant

PURPOSE

Reduce underarm wetness and perspiration

WARNINGS

For external use only

Do not use on broken or irritated skin

Stop use an ask a doctor if irritation or rash develops

KEEP OUT OF REACH OF CHILDREN

If swallowed, seek medical help or contact a poison control center immediately.

INSTRUCTIONS FOR USE

Remove cap, turn dial to raise product, apply evenly to underarms only. replace cap after use.

DOSAGE AND ADMINISTRATION

Stick antipirspirant deodorant

20% aluminum chlorohydrates

INDICATIONS AND USAGE

To reduce underarm wetness and perspiration

INACTIVE INGREDIENT

mineral oil, stearic acid, stearyl alcohol, talc, zinc palmitate, cyclopentasiloxane, hydrogenated castor oil, fragrance, silica, PPG-14, butyl ether, PEG-8 distearate, BHT.